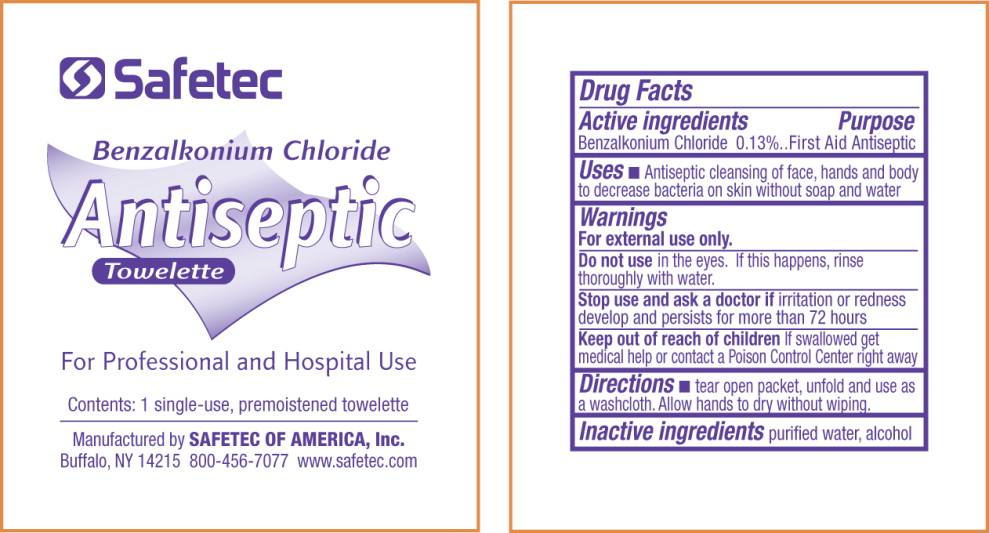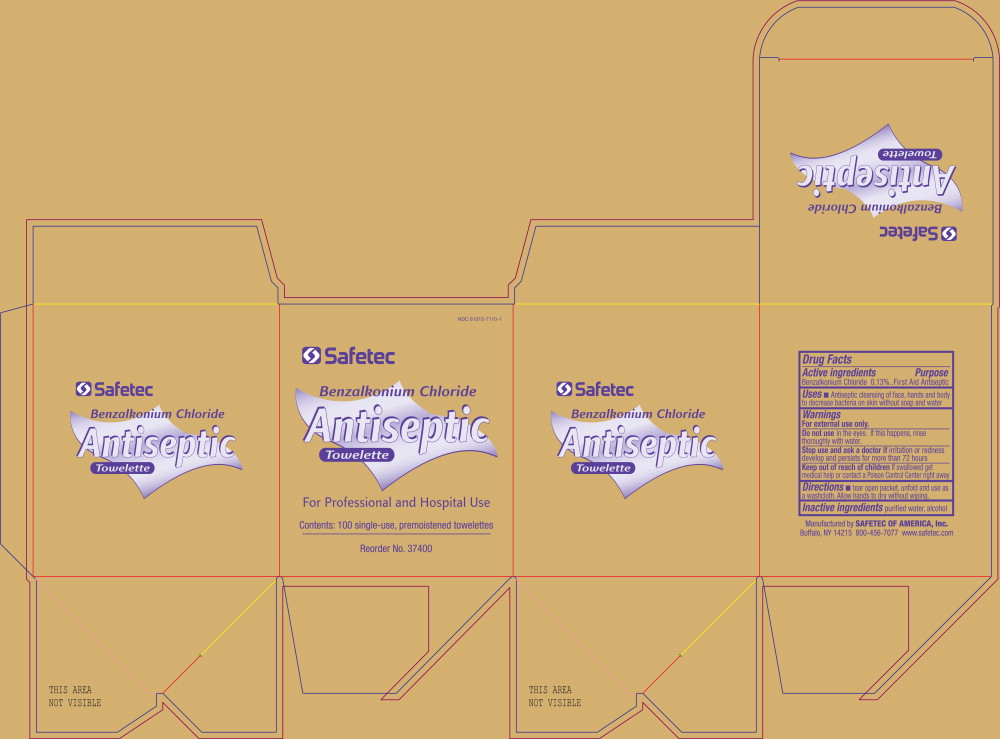 DRUG LABEL: Antiseptic
NDC: 61010-7110 | Form: LIQUID
Manufacturer: Safetec of America
Category: otc | Type: HUMAN OTC DRUG LABEL
Date: 20110712

ACTIVE INGREDIENTS: benzalkonium chloride 1.30 mL/1 L
INACTIVE INGREDIENTS: water; alcohol

ANTISEPTIC – Benzalkonium chloride liquid
Safetec of America

Benzalkonium Chloride
Antiseptic towelette

Drug Facts

Active Ingredients

Benzalkonium Chloride 0.13%

Purpose

First Aid Antiseptic

Uses

- Antiseptic cleansing of face, hands and body to decrease bacteria on skin without soap and water

Warnings

For external use only.

Do not use in the eyes. If this happens, rinse thoroughly with water.

Stop use and ask doctor if irritation or redness develop and persists for more than 72 hours

Keep out of reach of children If swallowed get medical help or contact a Poison Control Center right away

Directions

- tear open packet, unfold and use as a washcloth. Allow hands to dry without wiping.

Inactive ingredients

purified water, alcohol

PRINCIPAL DISPLAY PANEL – pouch label

Safetec

Benzalkonium Chloride
Antiseptic
Towelette

For Professional and Hospital Use

Contents: 1 single-use, premoistened towelette

Manufactured by SAFETEC OF AMERICA, Inc.
Buffalo, NY 14215 800-456-7077 www.safetec.com

PRINCIPAL DISPLAY PANEL – box label

NDC 61010-7110-1

Safetec

Benzalkonium Chloride
Antiseptic
Towelette

For Professional and Hospital Use

Contents: 100 single-use, premoistened towelettes

Reorder No. 37400